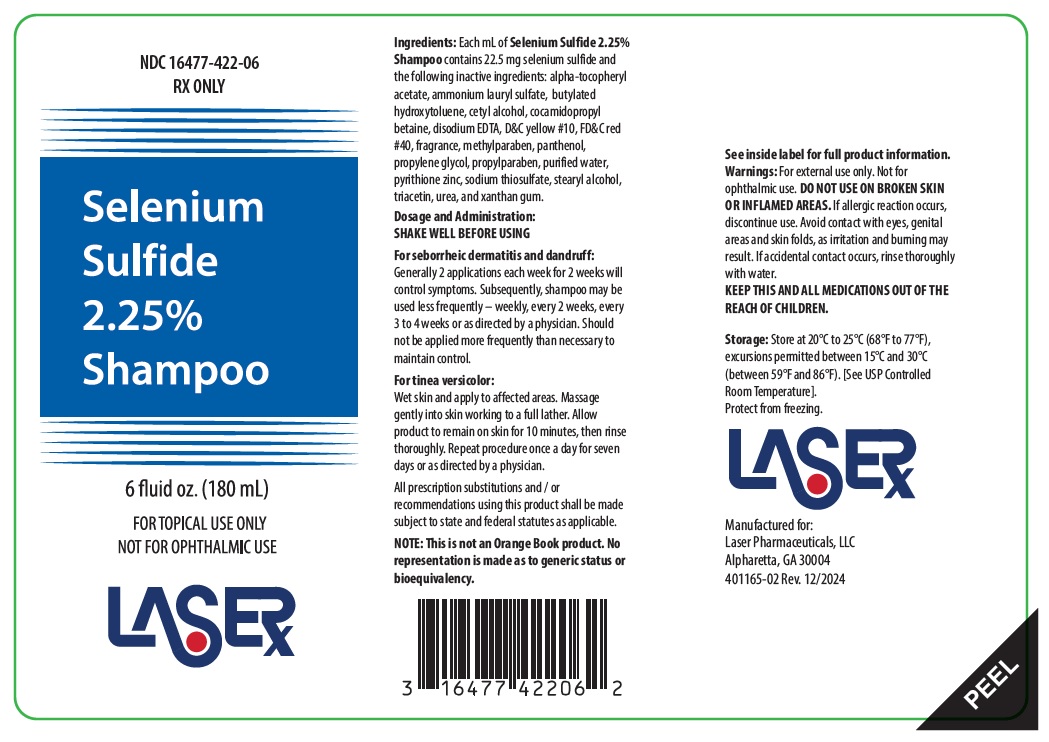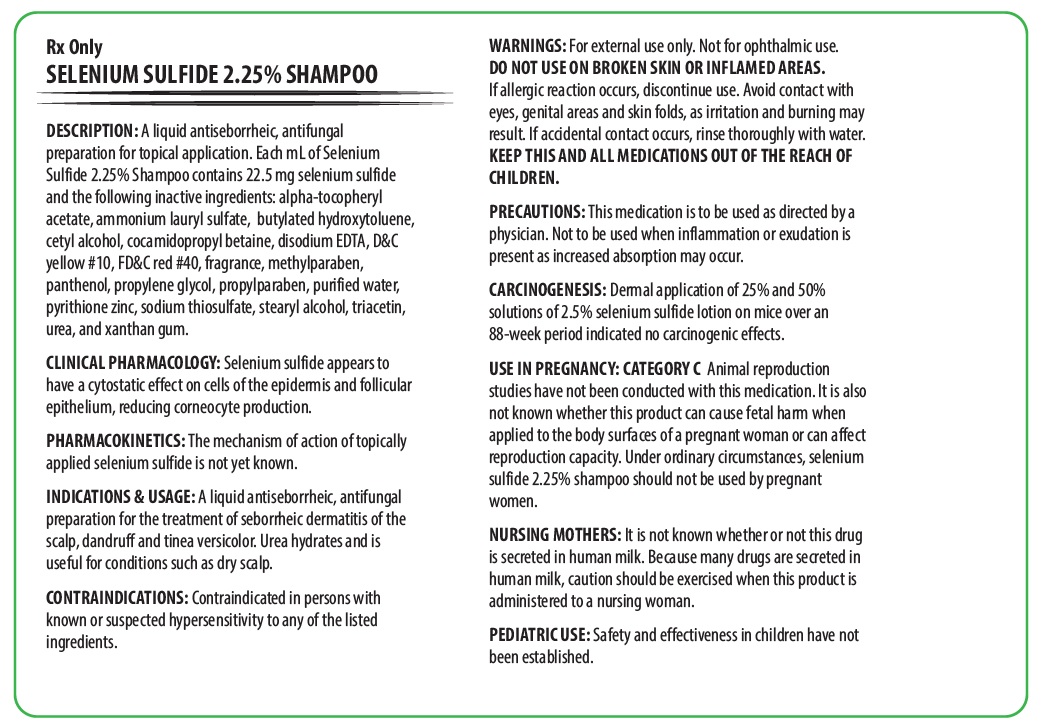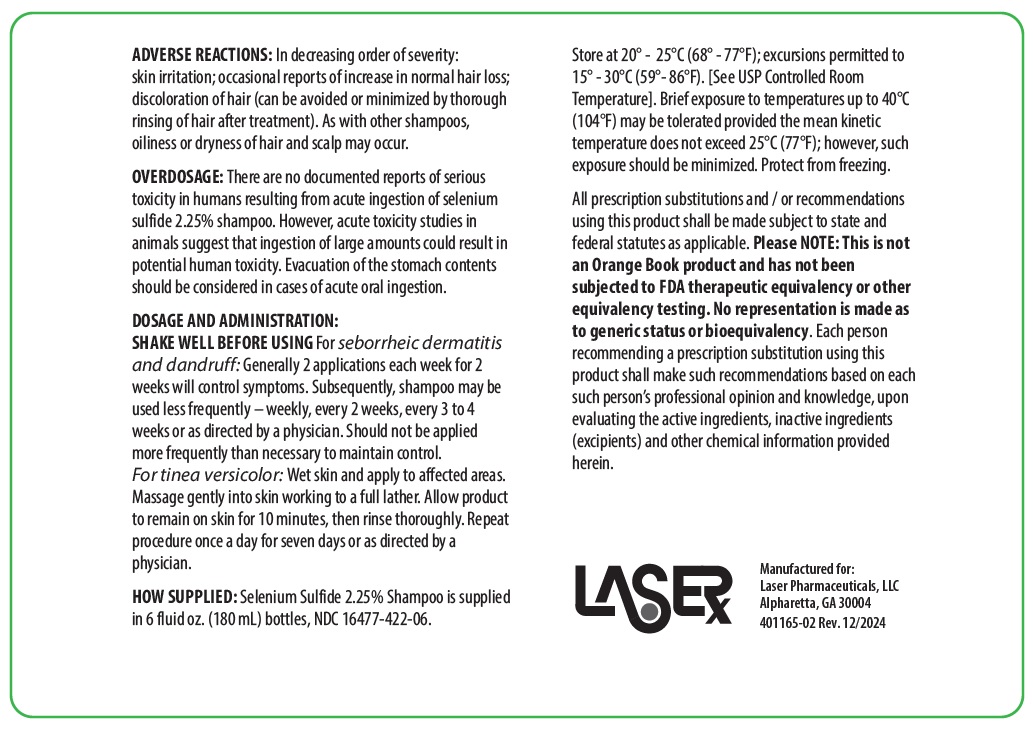 DRUG LABEL: Selenium Sulfide
NDC: 16477-422 | Form: SHAMPOO
Manufacturer: Laser Pharmaceuticals, LLC
Category: prescription | Type: HUMAN PRESCRIPTION DRUG LABEL
Date: 20251106

ACTIVE INGREDIENTS: SELENIUM SULFIDE 22.5 mg/1 mL
INACTIVE INGREDIENTS: PYRITHIONE ZINC; .ALPHA.-TOCOPHEROL ACETATE; UREA; BUTYLATED HYDROXYTOLUENE; CETYL ALCOHOL; AMMONIUM LAURYL SULFATE; COCAMIDOPROPYL BETAINE; EDETATE DISODIUM ANHYDROUS; METHYLPARABEN; PROPYLPARABEN; D&C YELLOW NO. 10; SODIUM THIOSULFATE; TRIACETIN; XANTHAN GUM; PANTHENOL; PROPYLENE GLYCOL; WATER; FD&C RED NO. 40; STEARYL ALCOHOL

Rx Only
Selenium Sulfide 2.25% Shampoo

DESCRIPTION

DESCRIPTION: A liquid antiseborrheic, antifungal preparation for topical application. Each mL of Selenium Sulfide 2.25% Shampoo contains 22.5 mg selenium sulfide, and the following inactive ingredients: Alpha-tocopheryl acetate, ammonium lauryl sulfate, butylated hydroxytoluene, cetyl alcohol, cocamidopropyl betaine, disodium EDTA, D&C yellow #10, FD&C red #40, fragrance, methylparaben, panthenol, propylene glycol, propylparaben, purified water, pyrithione zinc, sodium thiosulfate, stearyl alcohol, triacetin, urea, and xanthan gum.

CLINICAL PHARMACOLOGY

CLINICAL PHARMACOLOGY: Selenium sulfide appears to have a cytostatic effect on cells of the epidermis and follicular epithelium, reducing corneocyte production.

PHARMACOKINETICS

PHARMACOKINETICS: The mechanism of action of topically applied selenium sulfide is not yet known.

INDICATIONS AND USAGE

INDICATIONS & USAGE: A liquid antiseborrheic, antifungal preparation for the treatment of seborrheic dermatitis of the scalp, dandruff and tinea versicolor. Urea hydrates and is useful for conditions such as dry scalp.

CONTRAINDICATIONS

CONTRAINDICATIONS: Contraindicated in persons with known or suspected hypersensitivity to any of the listed ingredients.

WARNINGS

WARNINGS: For external use only. Not for ophthalmic use.

DO NOT USE ON BROKEN SKIN OR INFLAMED AREAS. If allergic reaction occurs, discontinue use. Avoid contact with eyes, genital areas and skin folds, as irritation and burning may result. If accidental contact occurs, rinse thoroughly with water. KEEP THIS AND ALL MEDICATIONS OUT OF THE REACH OF CHILDREN.

PRECAUTIONS

PRECAUTIONS: This medication is to be used as directed by a physician. Not to be used when inflammation or exudation is present as increased absorption may occur.

CARCINOGENESIS AND MUTAGENESIS AND IMPAIRMENT OF FERTILITY

CARCINOGENESIS: Dermal application of 25% and 50% solutions of 2.5% selenium sulfide lotion on mice over an 88-week period indicated no carcinogenic effects.

USE IN PREGNANCY:

CATEGORY C

Animal reproduction studies have not been conducted with this medication. It is also not known whether this product can cause fetal harm when applied to the body surfaces of a pregnant woman or can affect reproduction capacity. Under ordinary circumstances, selenium sulfide 2.25% shampoo should not be used by pregnant women.

NURSING MOTHERS

NURSING MOTHERS: It is not known whether or not this drug is secreted in human milk. Because many drugs are secreted in human milk, caution should be exercised when this product is administered to a nursing woman.

PEDIATRIC USE

PEDIATRIC USE: Safety and effectiveness in children have not been established.

ADVERSE REACTIONS

ADVERSE REACTIONS: In decreasing order of severity: skin irritation; occasional reports of increase in normal hair loss; discoloration of hair (can be avoided or minimized by thorough rinsing of hair after treatment). As with other shampoos, oiliness or dryness of hair and scalp may occur.

OVERDOSAGE

OVERDOSAGE: There are no documented reports of serious toxicity in humans resulting from acute ingestion of selenium sulfide 2.25% shampoo. However, acute toxicity studies in animals suggest that ingestion of large amounts could result in potential human toxicity. Evacuation of the stomach contents should be considered in cases of acute oral ingestion.

DOSAGE AND ADMINISTRATION:

SHAKE WELL BEFORE USING For seborrheic dermatitis and dandruff: Generally 2 applications each week for 2 weeks will control symptoms. Subsequently, shampoo may be used less frequently – weekly, every 2 weeks, every 3 to 4 weeks or as directed by a physician. Should not be applied more frequently than necessary to maintain control.
For tinea versicolor: Wet skin and apply to affected areas. Massage gently into skin working to a full lather. Allow product to remain on skin for 10 minutes, then rinse thoroughly. Repeat procedure once a day for seven days or as directed by a physician.

HOW SUPPLIED

HOW SUPPLIED: Selenium Sulfide 2.25% Shampoo is supplied in 6 fluid oz. (180 mL) bottles, NDC 16477-422-06. Store at 20° - 25°C (68° - 77°F), excursions permitted to 15° - 30°C (59° - 86°F). [See USP Controlled Room Temperature]. Brief exposure to temperatures up to 40°C (104°F) may be tolerated provided the mean kinetic temperature does not exceed 25°C (77°F); however, such exposure should be minimized. Protect from freezing.

All prescription substitutions and / or recommendations using this product shall be made subject to state and federal statutes as applicable. Please NOTE: This is not an Orange Book product and has not been subjected to FDA therapeutic equivalency or other equivalency testing. No representation is made as to generic status or bioequivalency. Each person recommending a prescription substitution using this product shall make such recommendations based on each such person’s professional opinion and knowledge, upon evaluating the active ingredients, inactive ingredients (excipients) and other chemical information provided herein.

Manufactured for:
Laser Pharmaceuticals, LLC
Alpharetta, GA 30004
401165-02 Rev 12/2024

PACKAGE LABEL

NDC 16477-422-06

Rx Only

Selenium

Sulfide

2.25%

Shampoo

6 fluid oz. (180 mL)

FOR TOPICAL USE ONLY

NOT FOR OPTHALMIC USE

LASER